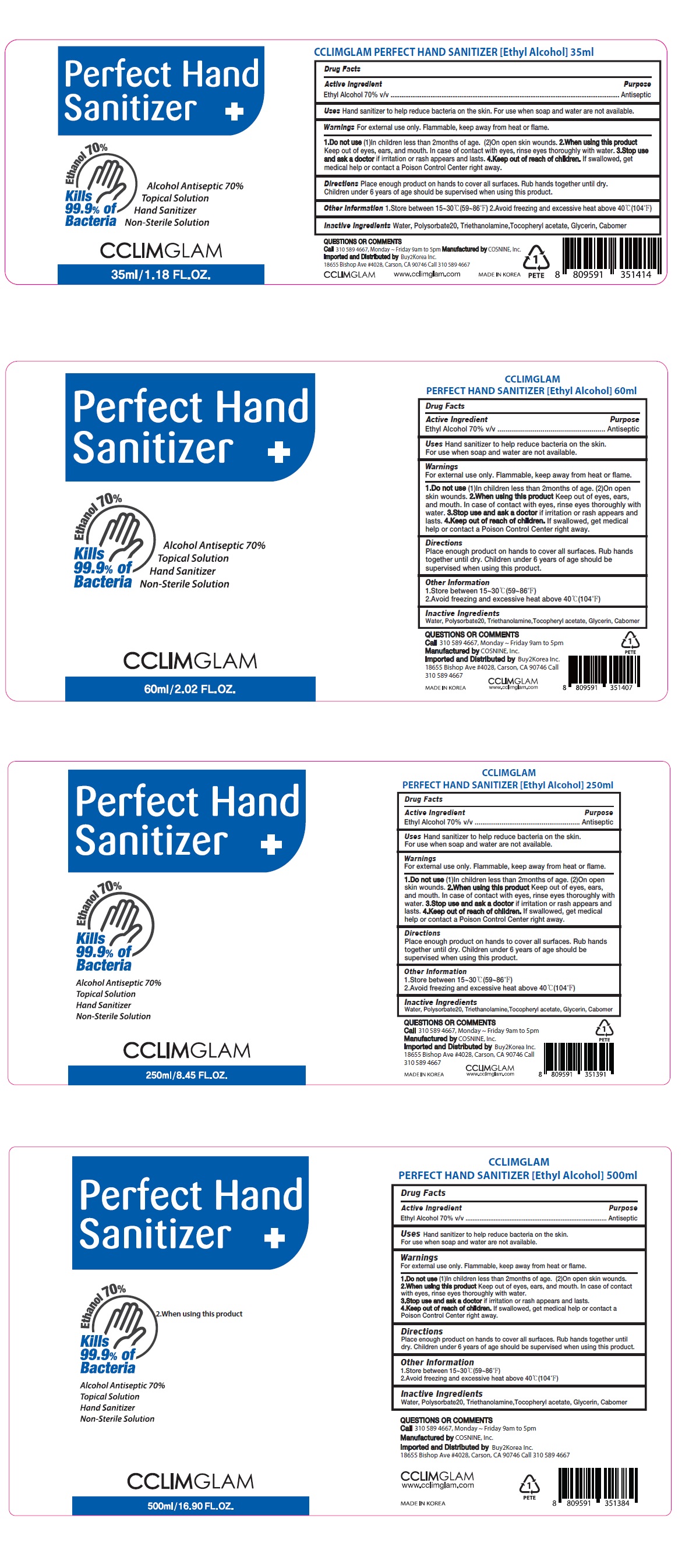 DRUG LABEL: Perfect Hand Sanitizer
NDC: 73330-0008 | Form: SOLUTION
Manufacturer: COSNINE, Inc.
Category: otc | Type: HUMAN OTC DRUG LABEL
Date: 20200405

ACTIVE INGREDIENTS: ALCOHOL 70 mL/100 mL
INACTIVE INGREDIENTS: WATER; POLYSORBATE 20; TROLAMINE; .ALPHA.-TOCOPHEROL ACETATE; GLYCERIN; CARBOMER HOMOPOLYMER, UNSPECIFIED TYPE

Perfect Hand Sanitizer +

Active Ingredient

Ethyl Alcohol 70% v/v

Purpose

Antiseptic

Uses

Hand sanitizer to help reduce bacteria on the skin.
For use when soap and water are not available.

Warnings

For external use only. Flammable, keep away from heat or flame.

1.Do not use (1) In children less than 2months of age. (2) On open skin wounds.
2. When using this product Keep out of eyes, ears, and mouth. In case of contact with eyes, rinse eyes thoroughly with water.
3. Stop use and ask a doctor if irritation or rash appears and lasts.

KEEP OUT OF REACH OF CHILDREN

4.Keep out of reach of children. If swallowed, get medical help or contact a Poison Control Center right away.

Directions

Place enough product on hands to cover all surfaces. Rub hands together until dry. Children under 6 years of age should be supervised when using this product.

Other Information

1. Store between 15~30°C(59~86°F)
2. Avoid freezing and excessive heat above 40°C(104°F)

Inactive Ingredients

Water, Polysorbate20, Triethanolamine,Tocopheryl acetate, Glycerin, Carbomer

Kills 99.9% of Bacteria

Alcohol Antiseptic 70%

Topical Solution

Non-Sterile Solution

QUESTIONS OR COMMENTS

Call 310 589 4667, Monday ~ Friday 9am to 5pm
Manufactured by COSNINE, Inc.
Imported and Distributed by Buy2Korea Inc.
18655 Bishop Ave #4028, Carson, CA 90746 Call 310 589 4667

CCLIMGLAM

www.cclimglam.com

MADE IN KOREA